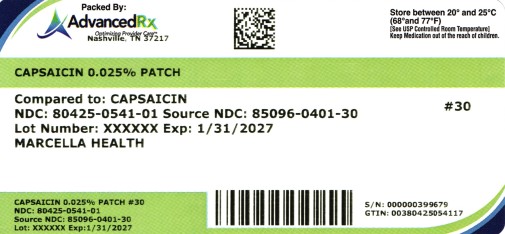 DRUG LABEL: Capsaicin 0.025%
NDC: 80425-0541 | Form: PATCH
Manufacturer: Advanced Rx of Tennessee, LLC
Category: otc | Type: HUMAN OTC DRUG LABEL
Date: 20250808

ACTIVE INGREDIENTS: CAPSAICIN 2.5 mg/10 g
INACTIVE INGREDIENTS: KAOLIN; TARTARIC ACID; WATER; DIHYDROXYALUMINUM AMINOACETATE ANHYDROUS; PROPYLENE GLYCOL; POLYACRYLIC ACID (250000 MW); SODIUM POLYACRYLATE (2500000 MW); TITANIUM DIOXIDE; CARBOXYMETHYLCELLULOSE SODIUM; POLYSORBATE 80; GLYCERIN; EDETATE DISODIUM; POVIDONE K90; HYDROXYACETOPHENONE; ISOPROPYL MYRISTATE

Capsaicin Patch
Capsaicin 0.025% | Pain Relieving Patch

Active Ingredient

Capsaicin 0.025% w/w

Purpose

External analgesic

Uses

For temporary relief of minor aches & pains of muscles & joints associated with:

- simple backache
- arthritis
- stratins
- bruises
- sprains

Warnings

For external use only

Do not use

- On wounds or damaged skin
- With a heating pad
- If you are allergic to any ingredients of this product

When using this product

- Use only as directed
- Avoid contact with the eyes, mucous membranes or rashes
- Do not bandage tightly

Stop use and ask a doctor if

- Rash, itching or excessive skin irratation develops
- Condition worsen
- Symptoms persist for more than 7 days
- Symptoms clear up and occur again within a few days

If pregnant or breast-feeding,

Ask a health professional before use

Keep out of reach of children.

If swallowed, get medical help or contact a Poison Control Center right away

Directions

Adult and Children 12 years of age and over:

- Clean and dry affected area
- Remove ﬁlm from patch and apply to the skin
- Apply 1 patch at a time to affected area, not more than 3 to 4 times daily
- Remove patch from the skin after at most 8-hour application

Children under 12 years of age:Consult a doctor

Other information

- Avoid storing product in direct sunlight
- Protect product from excessive moisture

Inactive Ingredients

Water, Glycerin, Polyacrylic Acid, Propylene Glycol, Sodium Polyacrylate, Isopropyl Myristate, Polysorbate 80, PVP, Hydroxyacetophenone, Dihydroxyaluminum Aminoacetate, L-Tartaric Acid, Titanium Dioxide, Carboxymethylcellulose Sodium, Kaolin, Edetate Disodium.

Questions or Comments

Call toll free (307) 410-3813 or info@marcellahealth.com